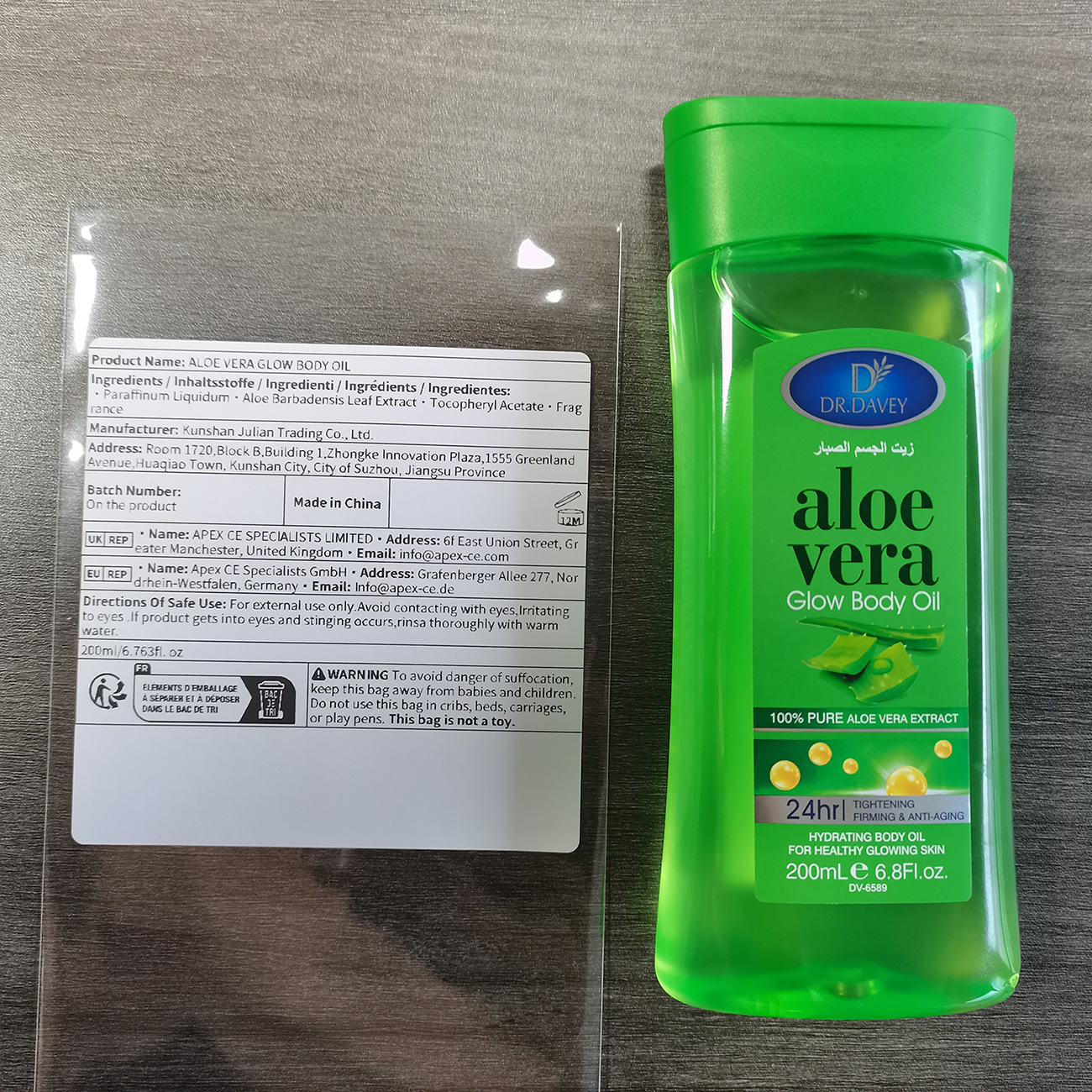 DRUG LABEL: ALOE VERA GLOW
NDC: 84551-011 | Form: OIL
Manufacturer: Kunshan Julian Trading Co., Ltd.
Category: otc | Type: HUMAN OTC DRUG LABEL
Date: 20240804

ACTIVE INGREDIENTS: ALOE BUETTNERI WHOLE 8 g/100 g
INACTIVE INGREDIENTS: FRAGRANCE 13576 0.2 g/100 g

ACTIVE INGREDIENT

Paraffinum Liquidum 90%

Aloe Barbadensis leaf Extract 8%

Tocopheryl Acetate 1.8%

Fragrance 0.2%

PURPOSE

ANTI-AGING

USAGE

Firming skin and anti-aging
If used daily, it can enhance the moisturizing effect of the body and make the skin look firmer

KEEP OUT OF REACH OF CHILDREN

If swallowed,get medical help or contact a Poison Control Center right away.

DO NOT USE

on damaged or broken skin

Stop use and ask a doctor if

rash occurs

When using this product

keep out of eyes.rinse with water to remove

WARNINGS

For extermal use only

DOSAGE & ADMINSTRATION

BID, 5-10g per dose
Ext.

Inactive ingredient section

Paraffinum Liquidum 90%